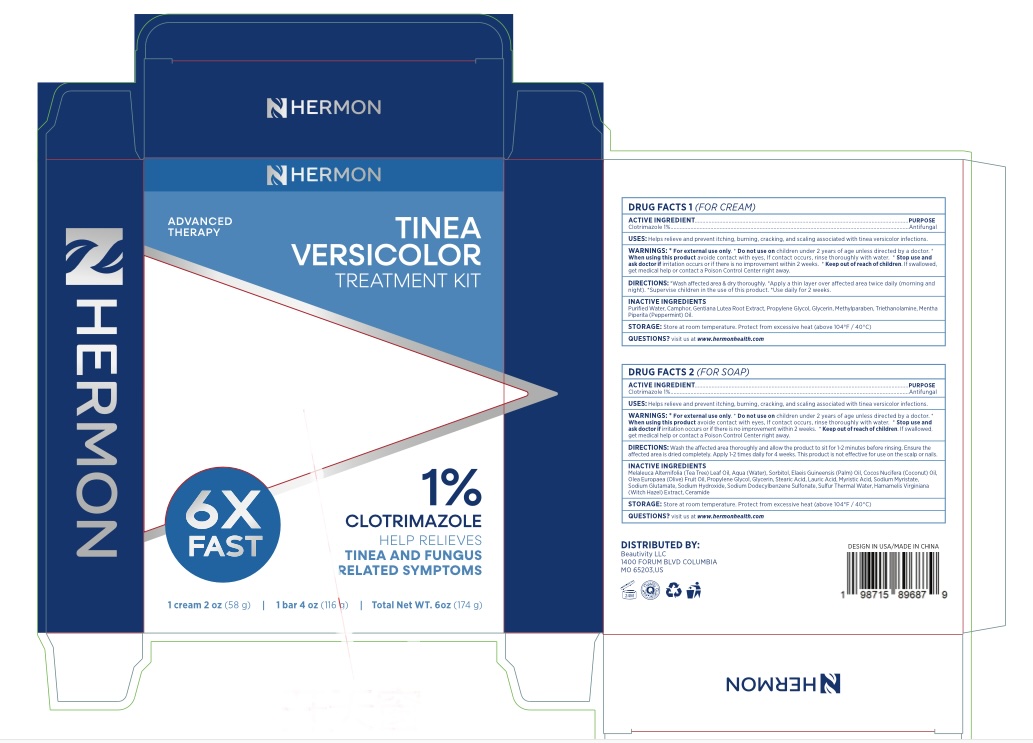 DRUG LABEL: Tinea Versicolor Treatment Bar
NDC: 85398-003 | Form: SOAP
Manufacturer: Beautivity LLC
Category: otc | Type: HUMAN OTC DRUG LABEL
Date: 20260302

ACTIVE INGREDIENTS: CLOTRIMAZOLE 10 mg/1 g
INACTIVE INGREDIENTS: STEARIC ACID; SODIUM DODECYLBENZENESULFONATE; WATER; SORBITOL; PROPYLENE GLYCOL; COCOS NUCIFERA (COCONUT) OIL; LAURIC ACID; MYRISTIC ACID; SODIUM HYDROXIDE; SULFUR; ELAEIS GUINEENSIS (PALM) OIL; OLEA EUROPAEA (OLIVE) FRUIT OIL; SODIUM GLUTAMATE; MELALEUCA ALTERNIFOLIA (TEA TREE) LEAF OIL; HAMAMELIS VIRGINIANA ROOT BARK/STEM BARK; SODIUM MYRISTATE; GLYCERIN

Update-85398-003-01

ACTIVE INGREDIENT

coltrimazole 1%

PURPOSE

antifungal

INDICATIONS AND USAGE

Helps relieve and prevent itching, burning, cracking, and scaling associated with tinea versicolor infections.

WARNINGS

For external use only

Do not use on Children under 2 years of age unless directed by a doctor.

When using this product avoid contact with eyes, if contact occurs, rinse thoroughly with water.

Stop use and ask doctor if irritation occurs or if there is no improvement within 2 weeks.

Keep out of reach of children. If swallowed, get medical help or contact a poison control center right away.

DOSAGE AND ADMINISTRATION

- Wash the affected area thoroughly and allow the product to sit for 1-2 minutes before rinsing.
- Ensure the affected area is dried completely.
- Apply 1-2 times daily for 4 weeks.
- This product is not effective for use on the scalp or nails.

INACTIVE INGREDIENT

Melaleuca Alternifolia (Tea Tree) Leaf Oil, Water, Sorbitol, Elaeis Guineensis (Palm) Oil, Cocos Nucifera (Coconut) Oil, Olea Europaea (Olive) Fruit Oil, Propylene Glycol, Glycerin, Stearic Acid, Lauric Acid, Myristic Acid, Sodium Myristate, Sodium Glutamate, Sodium Hydroxide, Sodium Dodecylbenzenesulfonate, Sulfur, Hamamelis Virginiana Root Bark, Ceramide

STORAGE AND HANDLING

Store at room temperature. Protect from excessive heat (above 104ºF / 40ºC)

QUESTIONS

visit us at www.hermonhealth.com